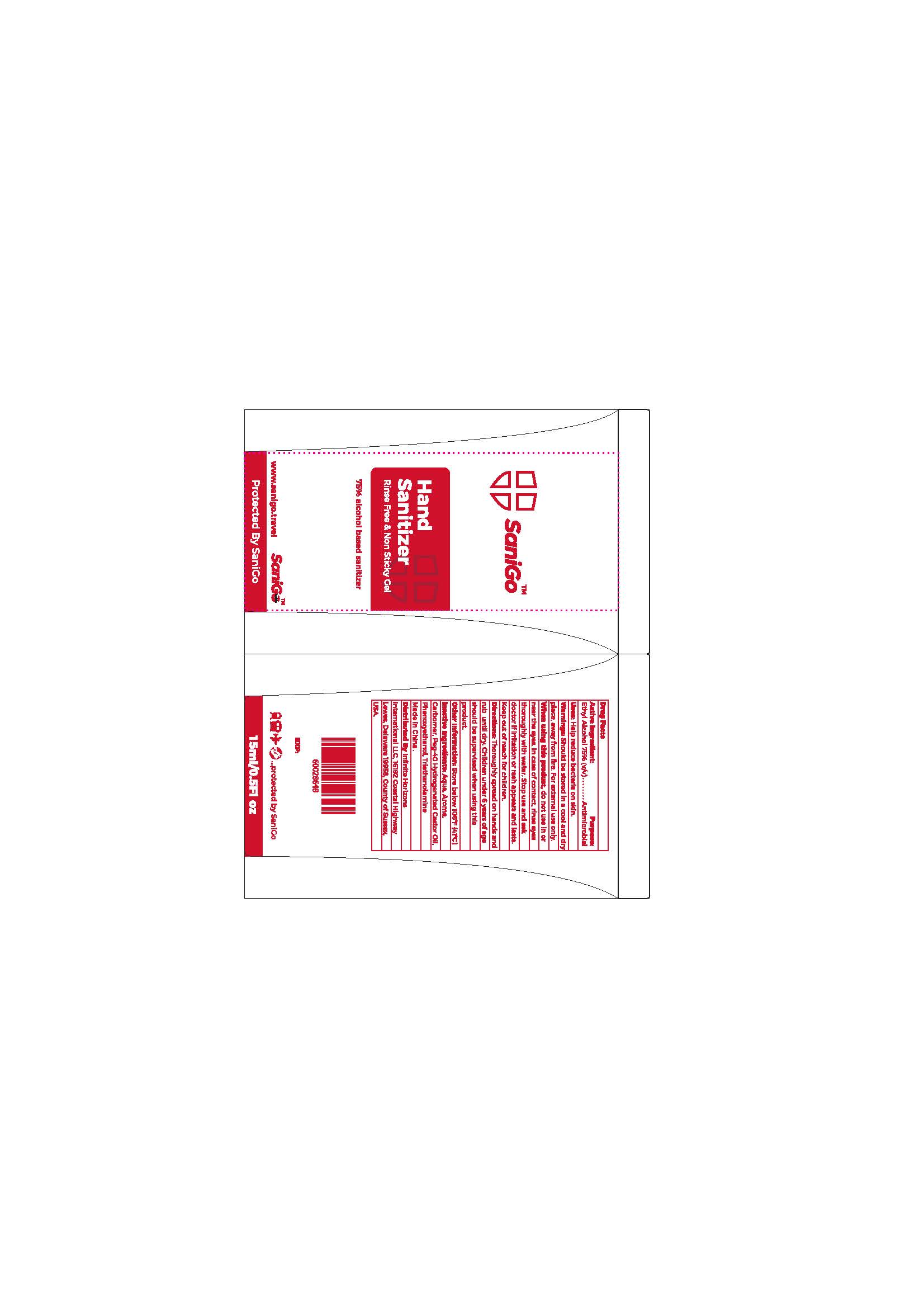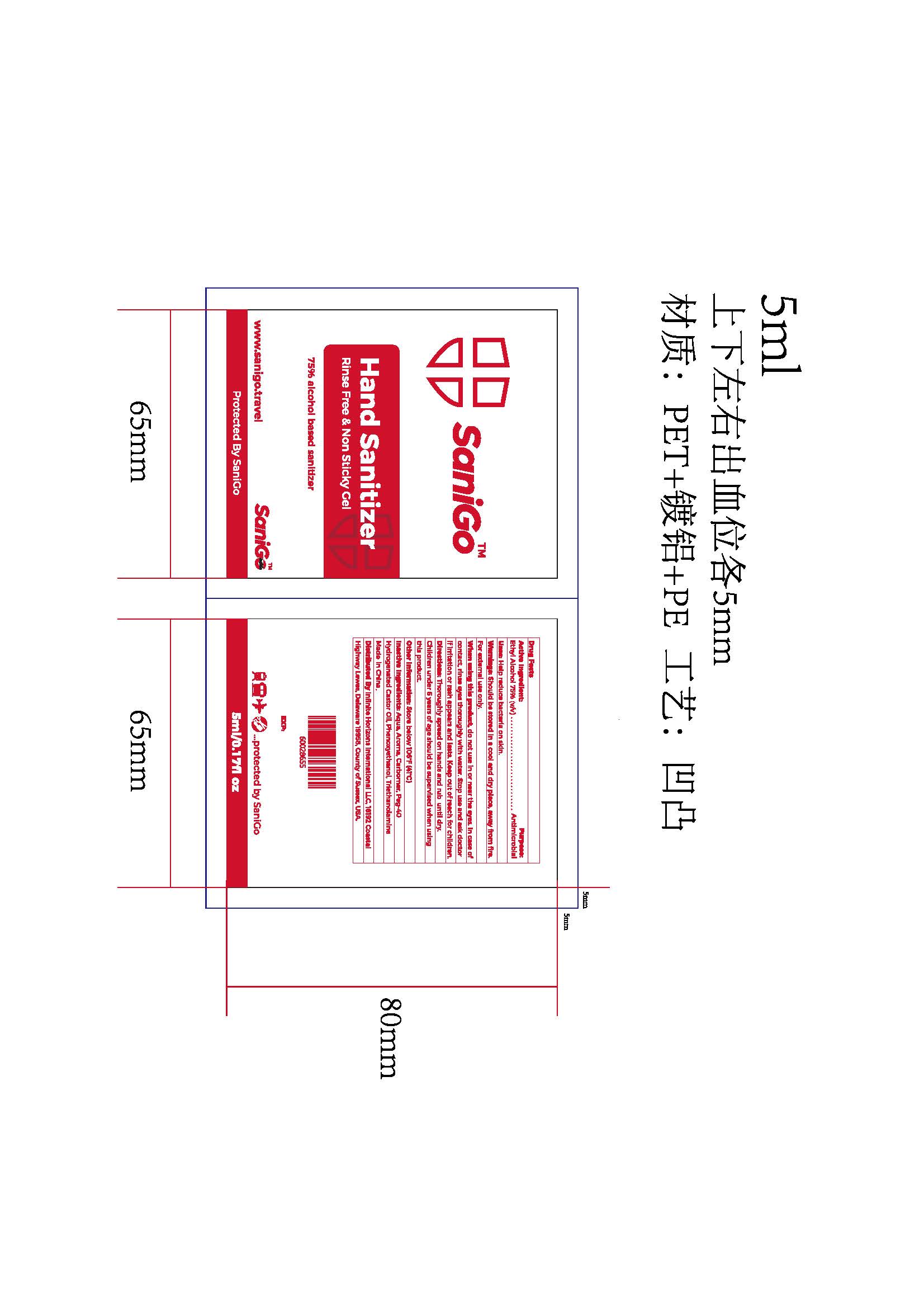 DRUG LABEL: Hand Sanitizer
NDC: 74761-015 | Form: GEL
Manufacturer: Guangzhou Oumiao Cosmetics Co. Ltd. 
Category: otc | Type: HUMAN OTC DRUG LABEL
Date: 20200922

ACTIVE INGREDIENTS: ALCOHOL 75 mL/100 mL
INACTIVE INGREDIENTS: PEG-40 CASTOR OIL; WATER; TROLAMINE; CARBOMER COPOLYMER TYPE A; PHENOXYETHANOL

74761-015
Hand Sanitizer

Active Ingredient

ETHYL ALCOHOL 75% Purpose : Antimicrobial

Purpose

Purpose : Antimicrobial

Uses

Uses: Help reduce bacteria on skin

Warnings

Warnings : Should be stored in a cool and dry place , away from fire .For external use only .

do not use in or near the eyes . In case of contact , rinse eyes thoroughly with water

When using this product , do not use in or near the eyes . In case of contact , rinse eyes thoroughly with water Stop use and ask doctor if irritation or rash appears and lasts . Keep out of reach for children

Stop use and ask doctor if irritation or rash appears and lasts .

Keep out of reach for children

Directions

Directions : Thoroughly spread on hands and rub until dry Children under 6 years of age should be supervised when using this product

Other information

Other Information : Store below 106'F (41C)

Distributed By Infinite Horizons International LLC , 16192 CoastalHighway Lewes , Delaware 19958 , County of Sussex , USA

Inactive ingredients

Inactive Ingredients : Aqua , Aroma , Carbomer , Peg-40Hydrogenated Castor Oil , Phenoxyethanol Triethanolamine